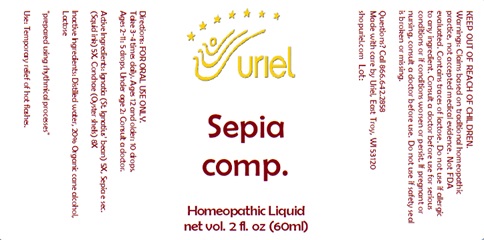 DRUG LABEL: Sepia comp.
NDC: 48951-8226 | Form: LIQUID
Manufacturer: Uriel Pharmacy Inc.
Category: homeopathic | Type: HUMAN OTC DRUG LABEL
Date: 20240709

ACTIVE INGREDIENTS: STRYCHNOS IGNATII SEED 5 [hp_X]/1 mL; SEPIA OFFICINALIS JUICE 5 [hp_X]/1 mL; OSTREA EDULIS SHELL 8 [hp_X]/1 mL
INACTIVE INGREDIENTS: LACTOSE, UNSPECIFIED FORM; WATER; ALCOHOL

Sepia comp.

INDICATIONS AND USAGE

Directions: FOR ORAL USE ONLY.

DOSAGE AND ADMINISTRATION

Take 3-4 times daily. Ages 12 and older: 10 drops. Ages 2-11: 5 drops. Under age 2: Consult a doctor.

ACTIVE INGREDIENT

Active Ingredients: Ignatia (St. Ignatius’ bean) 5X, Sepia e sec. (Squid ink) 5X, Conchae (Oyster shells) 8X

Inactive Ingredients: Distilled water, Organic cane alcohol, Lactose

PURPOSE

Use: Temporary relief of hot flashes.

KEEP OUT OF REACH OF CHILDREN.

WARNINGS

Warnings: Claims based on traditional homeopathic practice, not accepted medical evidence. Not FDA evaluated. Do not use if allergic to any ingredient. Consult a doctor before use for serious conditions or if conditions worsen or persist. Contains traces of lactose. If pregnant or nursing, consult a doctor before use. Do not use if safety seal is broken or missing.

QUESTIONS

Questions? Call 866.642.2858 Made with care by Uriel, East Troy, WI 53120 shopuriel.com Lot: